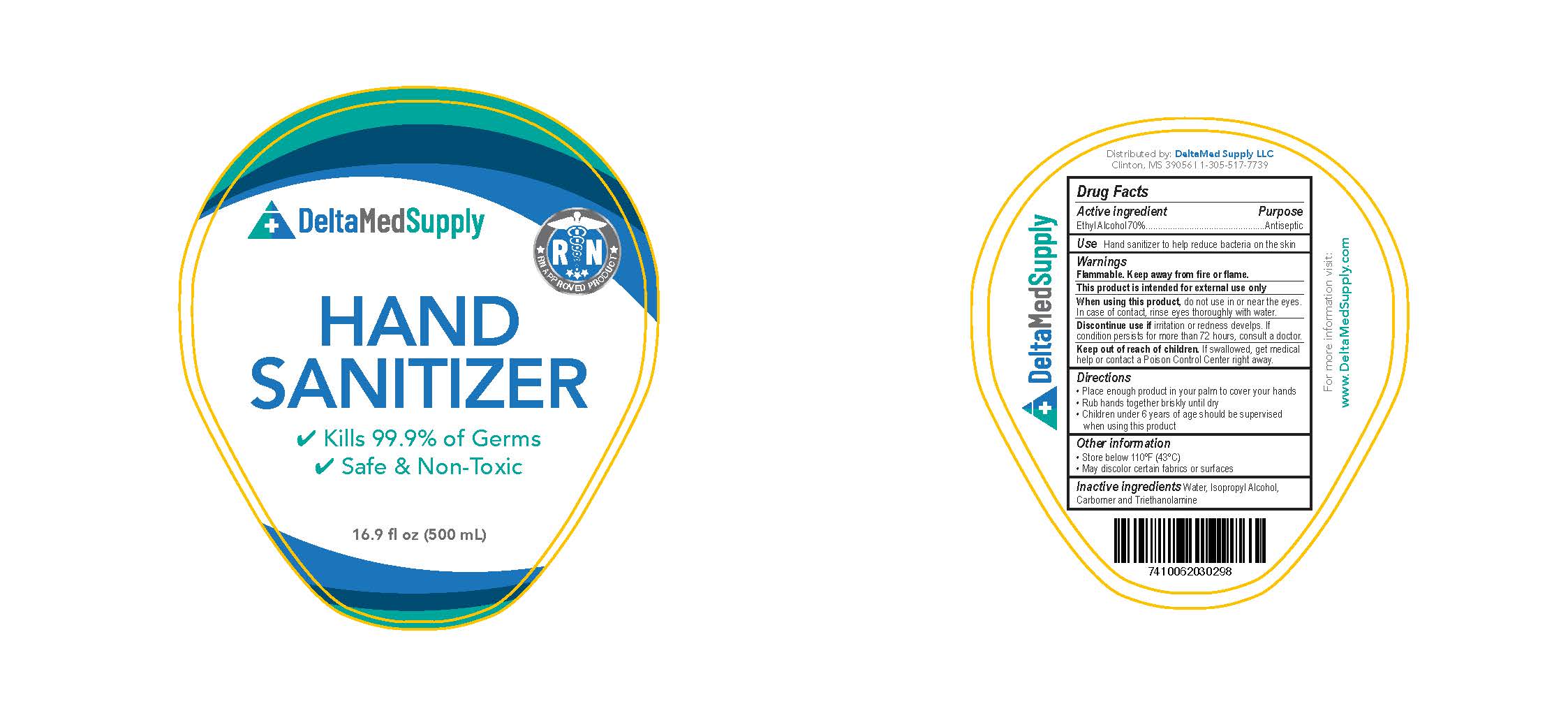 DRUG LABEL: HAND SANITIZER
NDC: 79727-000 | Form: GEL
Manufacturer: DELTAMED SUPPLY, LLC
Category: otc | Type: HUMAN OTC DRUG LABEL
Date: 20200803

ACTIVE INGREDIENTS: ALCOHOL 0.7 mL/1 mL
INACTIVE INGREDIENTS: ISOPROPYL ALCOHOL; WATER; TROLAMINE

Hand Sanitizer

Active ingredient

Ethyl Alcohol 70% Purpose: Antiseptic

Purpose

Antiseptic

Use

Hand sanitizer to help reduce bacteria on the skin

Warnings

Flammable. Keep away from fire or flame.
This product is intended for external use only

When using this product, do not use in or near the eyes.

In case of contact, rinse eyes thoroughly with water.

Discontinue use if irritation or redness develops. If condition persists for more than 72 hours, consult a doctor.

Keep out of reach of children

If swallowed, get medical help or contact a Poison Control Center right away.

Directions

- Place enough in your palm to cover your hands
- Rub hands together briskly until dry
- Children under 6 years of age should be supervised when using this product.

Other information

- Store below 110ºF (43ºC)
- May discolor certain fabrics or surfaces

Inactive Ingredients

Water, Isopropyl Alcohol, Carbomer and Triethanolamine

PACKAGE LABEL

500 ml NDC: 79727-000-02